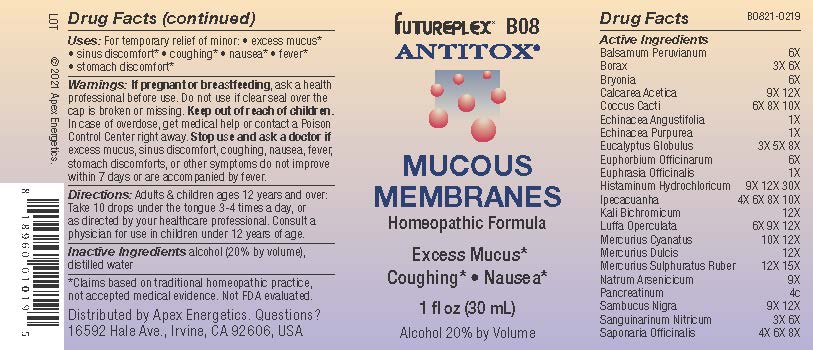 DRUG LABEL: B08
NDC: 63479-0208 | Form: SOLUTION/ DROPS
Manufacturer: Apex Energetics Inc.
Category: homeopathic | Type: HUMAN OTC DRUG LABEL
Date: 20240108

ACTIVE INGREDIENTS: EUPHRASIA STRICTA 1 [hp_X]/1 mL; HISTAMINE DIHYDROCHLORIDE 30 [hp_X]/1 mL; POTASSIUM DICHROMATE 12 [hp_X]/1 mL; SANGUINARINE NITRATE 6 [hp_X]/1 mL; SAPONARIA OFFICINALIS ROOT 8 [hp_X]/1 mL; BALSAM PERU 6 [hp_X]/1 mL; SODIUM BORATE 6 [hp_X]/1 mL; MERCURIC SULFIDE 15 [hp_X]/1 mL; ECHINACEA ANGUSTIFOLIA 1 [hp_X]/1 mL; SODIUM ARSENATE, DIBASIC, HEPTAHYDRATE 9 [hp_X]/1 mL; BRYONIA ALBA ROOT 6 [hp_X]/1 mL; CALCIUM ACETATE 12 [hp_X]/1 mL; PROTORTONIA CACTI 10 [hp_X]/1 mL; ECHINACEA PURPUREA 1 [hp_X]/1 mL; EUCALYPTUS GLOBULUS LEAF 8 [hp_X]/1 mL; IPECAC 10 [hp_X]/1 mL; LUFFA OPERCULATA FRUIT 12 [hp_X]/1 mL; MERCURIC CYANIDE 12 [hp_X]/1 mL; CALOMEL 12 [hp_X]/1 mL; PANCRELIPASE 4 [hp_C]/1 mL; SAMBUCUS NIGRA FLOWERING TOP 12 [hp_X]/1 mL; EUPHORBIA RESINIFERA RESIN 6 [hp_X]/1 mL
INACTIVE INGREDIENTS: WATER; ALCOHOL

B08

Active Ingredients
Balsamum Peruvianum | 6X
Borax | 3X 6X
Bryonia | 6X
Calcarea Acetica | 9X 12X
Coccus Cacti | 6X 8X 10X
Echinacea Angustifolia | 1X
Echinacea Purpurea | 1X
Eucalyptus Globulus | 3X 5X 8X
Euphorbium Officinarum | 6X
Euphrasia Officinalis | 1X
Histaminum Hydrochloricum | 9X 12X 30X
Ipecacuanha | 4X 6X 8X 10X
Kali Bichromicum | 12X
Luffa Operculata | 6X 9X 12X
Mercurius Cyanatus | 10X 12X
Mercurius Dulcis | 12X
Mercurius Sulphuratus Ruber | 12X 15X
Natrum Arsenicicum | 9X
Pancreatinum | 4C
Sambucus Nigra | 9X 12X
Sanguinarinum Nitricum | 3X 6X
Saponaria Officinalis | 4X 6X 8X

INDICATIONS AND USAGE

Uses:

For temporary relief of minor:

excess mucus*

sinus discomfort*

coughing*

nausea*

fever*

stomach discomfort*

*Claims based on traditional homeopathic practice, not accepted medical evidence. Not FDA evaluated

Warnings:

PREGNANCY OR BREAST FEEDING

If pregnant or breastfeeding, ask a health professional before use.

Do not use if clear seal over the cap is broken or missing.

Keep out of reach of children. In case of overdose, get medical help or contact a Poison Control Center right away.

Stop use and ask a doctor if excess mucus, sinus discomfort, coughing, nausea, fever, stomach discomforts, or other symptoms do not improve within 7 days or are accompanied by fever.

Directions:

Adults & children ages 12 years and over: Take 10 drops under the tongue 3-4 times a day, or as directed by your healthcare professional. Consult a physician for use in children under 12 years of age.

Inactive Ingredients

alcohol (20% by volume), distilled water

Distributed by Apex Energetics. Questions?

16592 Hale Ave., Irvine, CA 92606, USA

PACKAGE LABEL

FUTUREPLEX® B08

ANTITOX®

MUCOUS MEMBRANES

Homeopathic Formula

Excess Mucus*

Coughing* Nausea*

1 fl oz (30 mL)

Alcohol 20% by Volume